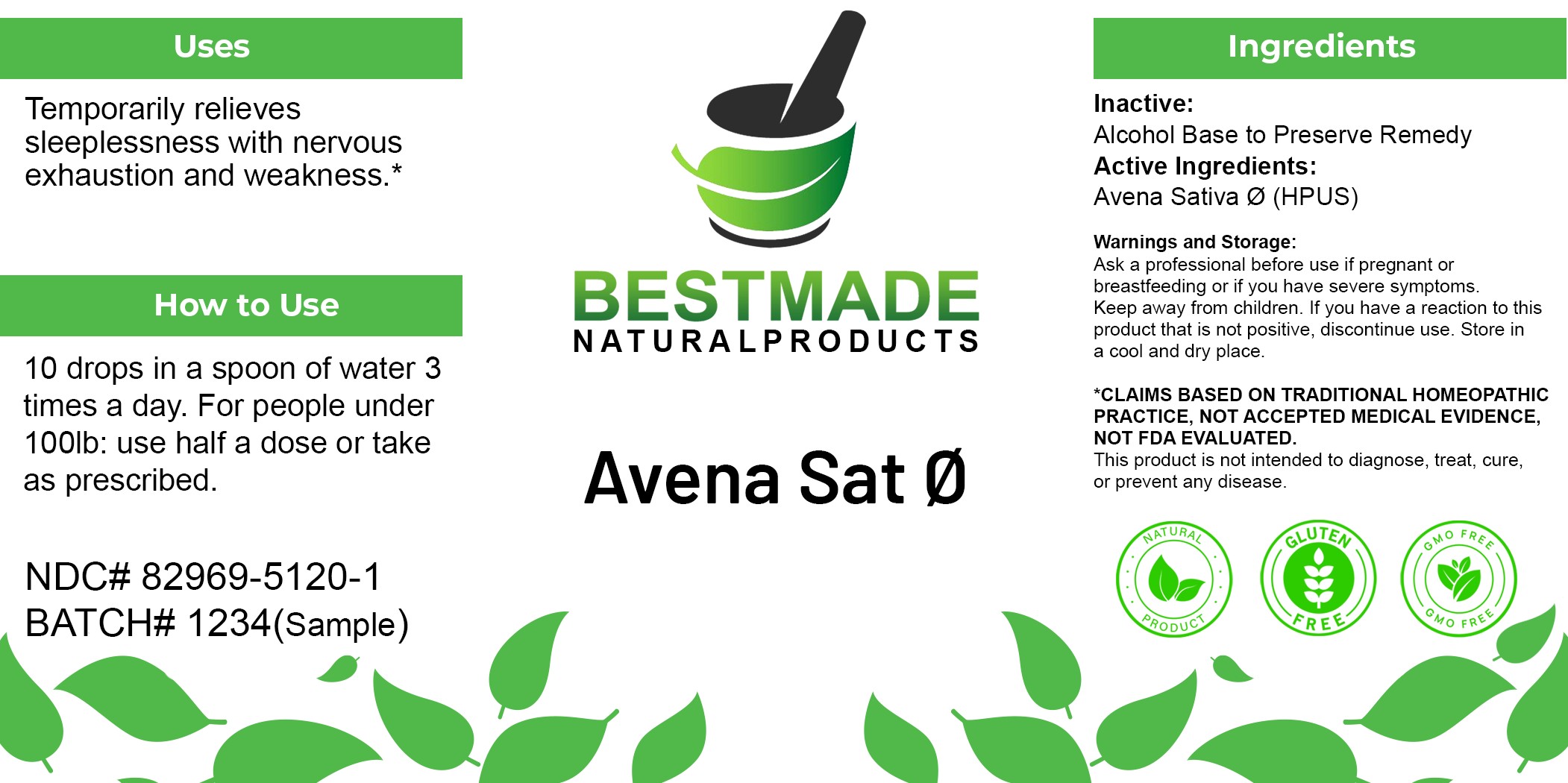 DRUG LABEL: Bestmade Natural Products Avena Sat
NDC: 82969-5120 | Form: LIQUID
Manufacturer: Bestmade Natural Products
Category: homeopathic | Type: HUMAN OTC DRUG LABEL
Date: 20250605

ACTIVE INGREDIENTS: AVENA SATIVA FLOWERING TOP 1 [hp_M]/1 mL
INACTIVE INGREDIENTS: WATER 0.3 mL/1 mL; ALCOHOL 0.7 mL/1 mL

Avena Sativa Tinc

Inactive Ingredient: Alcohol base to preserve product.

INDICATIONS AND USAGE

Use: Temporarily relieves sleeplessness with nervous exhaustion and weakness.*

PURPOSE

Use: Temporarily relieves sleeplessness with nervous exhaustion and weakness.*

DOSAGE AND ADMINISTRATION

Dosage Instructions: 10 drops in a spoon of water 3 times a day. For people under 100lb: use half a dose or take as prescribed.

Active Ingredient: Avena Sativa Ø (HPUS)

KEEP OUT OF REACH OF CHILDREN

Warnings and Storage:

Ask a professional before use if pregnant or breastfeeding or if you have severe symptoms. Keep away from children. If you have a reaction to this product that is not positive, discontinue use. Store in a cool and dry place.

*CLAIMS BASED ON TRADITIONAL HOMEOPATHIC PRACTICE, NOT ACCEPTED MEDICAL EVIDENCE, NOT FDA EVALUATED. This product is not intended to diagnose, treat, cure, or prevent any disease.

Warnings and Storage:

Ask a professional before use if pregnant or breastfeeding or if you have severe symptoms. Keep away from children. If you have a reaction to this product that is not positive, discontinue use. Store in a cool and dry place.

*CLAIMS BASED ON TRADITIONAL HOMEOPATHIC PRACTICE, NOT ACCEPTED MEDICAL EVIDENCE, NOT FDA EVALUATED. This product is not intended to diagnose, treat, cure, or prevent any disease.

Entire Package Label